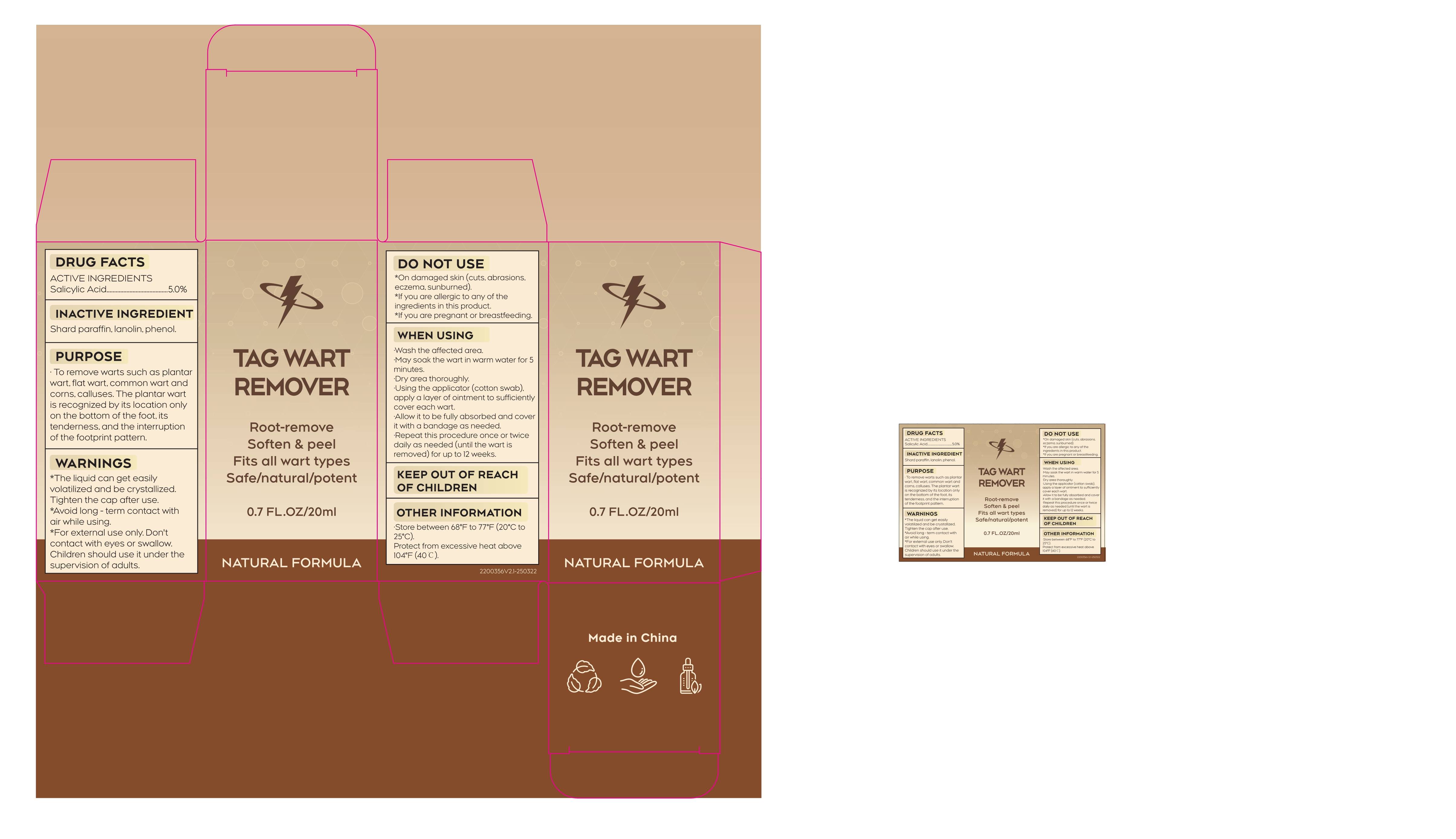 DRUG LABEL: TAG  WART REMOVER
NDC: 84023-117 | Form: LIQUID
Manufacturer: Shenzhen Yangan Technology Co., Ltd.
Category: otc | Type: HUMAN OTC DRUG LABEL
Date: 20250421

ACTIVE INGREDIENTS: SALICYLIC ACID 5 mg/100 mL
INACTIVE INGREDIENTS: PHENOL; PARAFFIN; LANOLIN

20ml

ACTIVE INGREDIENT

Salicyic Acid......................5.0%

PURPOSE

To remove warts such as plantar wart, flat wart, common wart and corns, calluses.

INDICATIONS AND USAGE

To remove warts such as plantarvart.flat wart,common wart andcorns,calluses.
The plantar wart is recognized by it location only on the bottom of thefoot it’s tenderness，and the interruption of the footprint pattern

DOSAGE AND ADMINISTRATION

Wash the affected area.
May soak the wart in warmwater for 5 minutes.
Dry area thoroughly.
Using the applicator(cottonswab）apply a layer ofointment to sufficiently cover each wart
Allow it to fully absorb andcover it with a bandage asneeded.
Repeat this procedure onceor twice daily as needed (until the wart is removed) for upto12weeks

DO NOT USE

·On damaged skin(cuts,abrasions,eczema sunburn.

·f you are allergic to any of theingredients in this product.

·lf you are pregnant or breastfeeding

KEEP OUT OF REACH OF CHILDREN

WHEN USING

·To remove warts such as plantarvart.flat wart,common wart andcorns,calluses.

·The plantar wart is recognized by it location only on the bottom of thefoot it’s tenderness，and the interruption of the footprint pattern

WARNINGS

·The liquid can get easily volatilized crystallized. tighten the cap after use.

·Avoid long-term contact with air while using.

·For external use only, don’t contact with eyes or swallow. Children should use it under the supervision of adults.

ASK DOCTOR

See a doctor as you may have a more serious skin condition.

OTHER SAFETY INFORMATION

Store between 68°F to 77°F（20°Cto25°C).

Protect from excessive heatabove 104°F（40°C）

INACTIVE INGREDIENT

Shard paraffin, lanolin, phenol